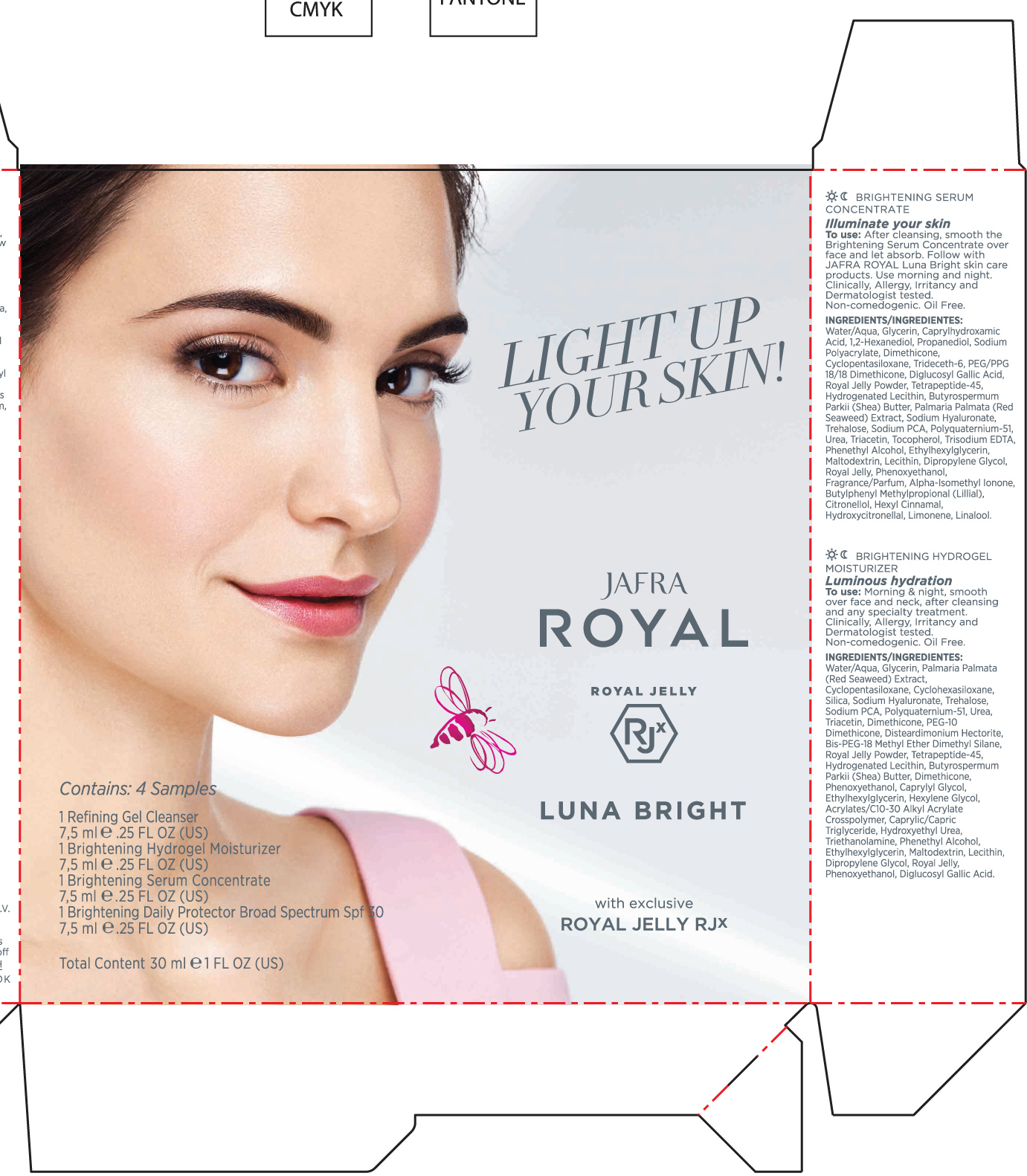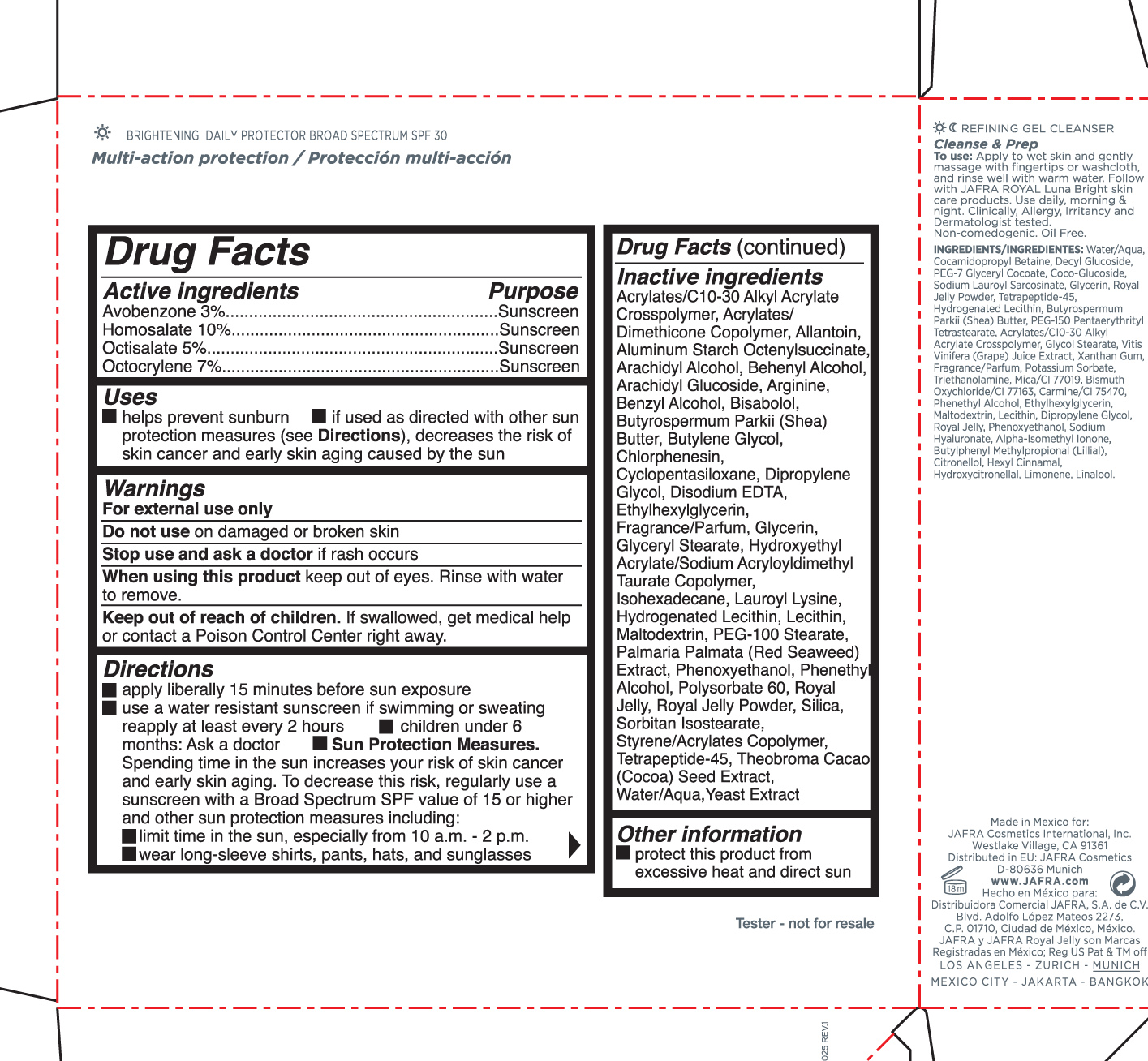 DRUG LABEL: Jafra Royal Luna Bright Kit
NDC: 68828-285 | Form: KIT | Route: TOPICAL
Manufacturer: JAFRA COSMETICS INTERNATIONAL INC
Category: otc | Type: HUMAN OTC DRUG LABEL
Date: 20190115

ACTIVE INGREDIENTS: AVOBENZONE 3 g/100 mL; HOMOSALATE 10 g/100 mL; OCTISALATE 5 g/100 mL; OCTOCRYLENE 7 g/100 mL
INACTIVE INGREDIENTS: HYDROXYETHYL ACRYLATE/SODIUM ACRYLOYLDIMETHYL TAURATE COPOLYMER (100000 MPA.S AT 1.5%); LAUROYL LYSINE; CARBOMER COPOLYMER TYPE A (ALLYL PENTAERYTHRITOL CROSSLINKED); ARACHIDYL ALCOHOL; DOCOSANOL; ARGININE; LEVOMENOL; SHEA BUTTER; BUTYLENE GLYCOL; CHLORPHENESIN; ETHYLHEXYLGLYCERIN; PHENOXYETHANOL; ALLANTOIN, (+)-; ALUMINUM STARCH OCTENYLSUCCINATE; ARACHIDYL GLUCOSIDE; BENZYL ALCOHOL; CYCLOMETHICONE 5; EDETATE DISODIUM; ISOHEXADECANE; HYDROGENATED SOYBEAN LECITHIN; LECITHIN, SOYBEAN; MALTODEXTRIN; PEG-100 STEARATE; DULSE; POLYSORBATE 60; ROYAL JELLY; SILICON DIOXIDE; PEG-20 SORBITAN ISOSTEARATE; COCOA; GLYCERYL MONOSTEARATE; GLYCERIN; WATER; DIPROPYLENE GLYCOL; PHENYLETHYL ALCOHOL

Jafra Royal Luna Bright Kit

Active Ingredients Purpose

Avobenzone 3% Sunscreen

Homosalate 10% Sunscreen

Octisalate 5% Sunscreen

Oxybenzone 7% Sunscreen

Uses

helps prevent sunburn
if used as directed with other sun protection measures (see Directions), decreases the risk of skin cancer and early skin aging caused by the sun

Keep out of reach of children. If product is swallowed, get medical help or contact a Poison Control Center right away.

Stop use and ask a doctor if rash occurs.

Warnings

For external use only

Do not use on damaged or broken skin

When using this product keep out of eyes. Rinse with water to remove.

Directions

apply liberally 15 minutes before sun exposure
use a water resistant sunscreen if swimming or sweating
reapply at least every 2 hours
children under 6 months: Ask a doctor
Sun Protection Measures. Spending time in the sun increases your risk of skin cancer and skin aging. to decrease

this risk, regularly use a sunscreen with a Broad Spectrum SPFvalue of 15 or higher and other sun measures including;

limit time in the sun, especially from 10 a.m. - 2 p.m.

wear long-sleeve shirts, pants, hats, and sunglasses

Inactive ingredients

Acrylates/C10-30 Alkyl Acrylate Crosspolymer, Acrylates/Dimethicone Copolymer, Allantoin, Aluminum Starch octenylsuccinate, Arachidyl Alcohol, Behenyl Alcohol, Arachidyl Glucoside, Arginine, Benzyl Alcohol, Bisabolol, Butyrospermum Parkii (Shea) Butter, Butylene Glycol, Chlorphenesin, Cyclopentasiloxane, Dipropylene Glycol, Disodium EDTA, Ethylhexylglycerin, Fragrance/Parfum, Glycerin, Glyceryl Stearate, Hydroxyethyl Acrylate/Sodium Acryloyldimethyl Taurate Copolymer, Isohexadecane, Lauroyl Lysine, Hydrogenated Lecithin, Lecithin, Maltodextrin, PEG-100 stearate, Palmaria Palmata (red seaweed) extract, Phenoxyethanol, Phenenthyl Alcohol, Polysorbate, Royal Jelly, Royal Jelly Powder, Silica, Sorbitan Isostearate, Styrene/Acrylates Copolymer, Tetrapeptide-45 , Theobroma Cacao (Cocoa) Seed Extract, Water/Aqua, Yeast Extract

PACKAGE LABEL

Jafra Royal

Royal Jelly

Luna Bright

Contains 4 samples

1 Refining Gel Cleanser

7.5ml .25 FL OZ

1 Brightening Hydrogel Moisturizer

7.5ml .25 FL OZ

1 Brightening Serum Concentrate

7.5ml .25 FL OZ

1 Brightening Daily Protector Broad SpectrumSPF 30

7.5ml .25 FL OZ

Total Contents 30ml 1 FL OZ